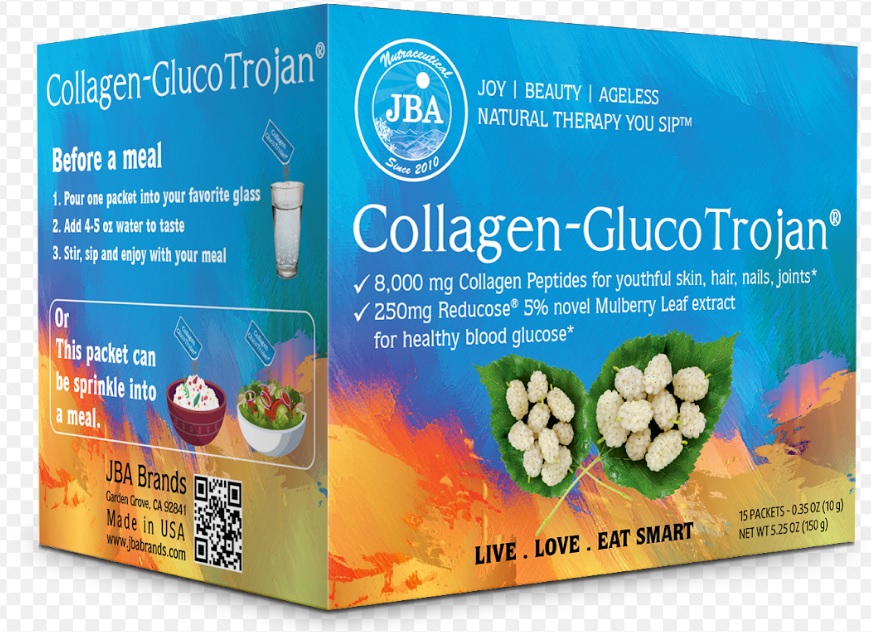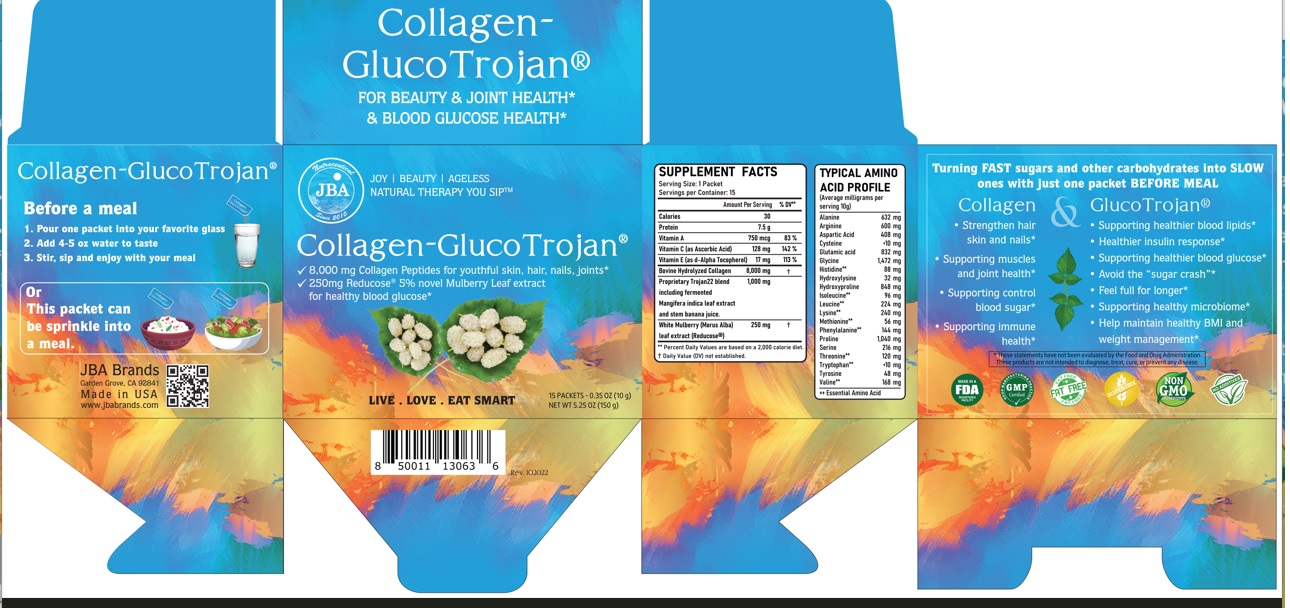 DRUG LABEL: JBA Collagen-GlucoTrojan
NDC: 13411-898 | Form: POWDER
Manufacturer: Advanced Pharmaceutical Services, Inc. Dba Affordable Quality Pharmaceuticals
Category: other | Type: DIETARY SUPPLEMENT
Date: 20230130

ACTIVE INGREDIENTS: VITAMIN A 750 ug/10 g; ASCORBIC ACID 128 mg/10 g; .ALPHA.-TOCOPHEROL 17 mg/10 g; BOVINE TYPE I COLLAGEN 8000 mg/10 g; MANGO 500 mg/10 g; BANANA 500 mg/10 g; WHITE MULBERRY 250 mg/10 g

Identity

Dietary supplement

Warnings

- Keep out of reach of children
- Do not exceed the recommended dose
- Consult your physician prior to using this product if you are pregnant, nursing, or if you are taking blood glucose lowering medication, or have a medical condition.

Direction

Before a meal:
1. Pour one packet into your favorite glass
2. Add 4-5 oz water to taste
3. Stir, sip and enjoy with your meal

Or
This packet can be sprinkle into a meal

Safe handling warning

- Store in a cool, dry place

Health claim section

JBA® Collagen-GlucoTrojan®
For Beauty & Joint Health * & Blood Glucose Health*

- 8,000 mg Collagen Peptides for youthful skin, hair, nails, joint*
- 250 mg Reducose® 5% novel Mulberry Leaf extract for healthy blood glucose*

Turning FAST sugars and other carbohydrates into SLOW ones with just one packet BEFORE MEAL
Collagen

- Strengthen hair skin and nails*
- Supporting muscles and joint health*
- Supporting control blood sugar*
- Supporting immune health*

GlucoTrojan

- Supporting healthier blood lipids*
- Healthier insulin response*
- Supporting healthier blood glucose*
- Avoid the “sugar crash”*
- Feel full for longer*
- Supporting heathy microbiome*
- Help maintain healthy BMI and weight management*

* These statements have not been evaluated by the Food & Drug Administration. This product is not intended to diagnose, treat, cure, or prevent any disease.